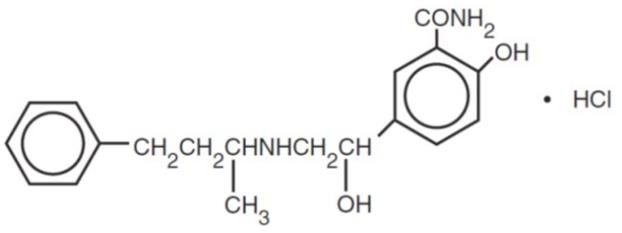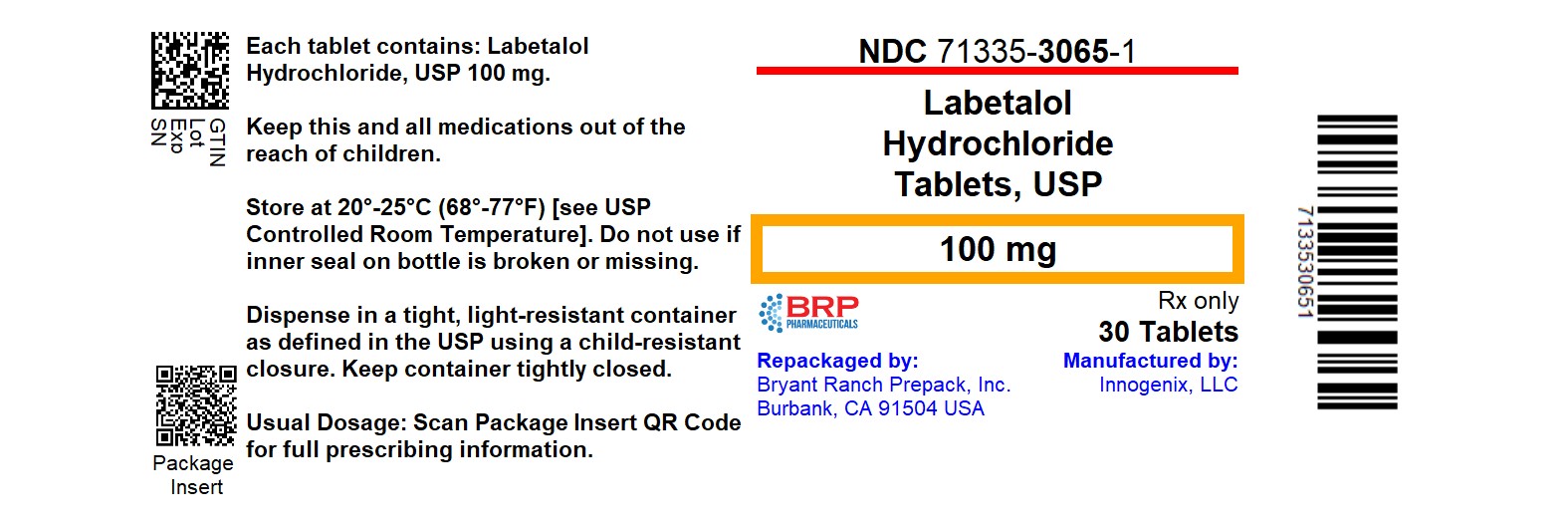 DRUG LABEL: Labetalol Hydrochloride
NDC: 71335-3065 | Form: TABLET, FILM COATED
Manufacturer: Bryant Ranch Prepack
Category: prescription | Type: HUMAN PRESCRIPTION DRUG LABEL
Date: 20260206

ACTIVE INGREDIENTS: LABETALOL 100 mg/1 1
INACTIVE INGREDIENTS: ANHYDROUS LACTOSE; CARNAUBA WAX; HYPROMELLOSE, UNSPECIFIED; MAGNESIUM STEARATE; POLYETHYLENE GLYCOL, UNSPECIFIED; POLYSORBATE 80; STARCH, CORN; FERRIC OXIDE RED; TITANIUM DIOXIDE; FERRIC OXIDE YELLOW

HIGHLIGHTS OF PRESCRIBING INFORMATION

These highlights do not include all the information needed to use LABETALOL HYDROCHLORIDE TABLETS safely and effectively. See full prescribing information for LABETALOL HYDROCHLORIDE TABLETS.
LABETALOL HYDROCHLORIDE tablets, for oral use.
Initial U.S. Approval: 1984

1 INDICATIONS AND USAGE

Labetalol Hydrochloride Tablets are a beta adrenergic blocker indicated for the treatment of hypertension, to lower blood pressure. Lowering blood pressure reduces the risk of fatal and nonfatal cardiovascular events, primarily strokes and myocardial infarctions. (1)

2 DOSAGE AND ADMINISTRATION

- The recommended initial dosage is 100 mg twice daily, alone or added to a diuretic regimen. Titrate in increments of 100 mg twice daily every 2 or 3 days. Maintenance dosage is between 200 and 400 mg twice daily. (2.1)
- Severe Hypertension: May require from 1,200 to 2,400mg per day, with or without thiazide diuretics. Titrate in increments not to exceed 200 mg twice daily. (2.2)
- Elderly patients: Initiate at 100 mg twice daily. Titrate in increments of 100 mg twice daily as required for blood pressure control. Many elderly patients will require between 100 and 200 mg twice daily. (2.3)

3 DOSAGE FORMS AND STRENGTHS

Tablets: 100 mg, 200 mg, and 300 mg tablets (3)

4 CONTRAINDICATIONS

- Bronchial asthma or obstructive airway disease (4)
- Overt cardiac failure (4)
- Greater‑than‑first‑degree heart block (4)
- Cardiogenic shock (4)
- Severe bradycardia (4)
- Non-dihydropyridine calcium-channel antagonists (4)

5 WARNINGS AND PRECAUTIONS

- Monitor patients for symptomatic postural hypotension and syncope after initial dosing or dose increments. (5.1)
- Monitor heart rate and rhythm for bradycardia, including sinus pause, heart block, severe bradycardia, and cardiac arrest in patients receiving Labetalol Hydrochloride Tablets. (5.2)
- Beta-blockade can depress myocardial contractility and precipitating more severe failure. Avoid use in patients with overt heart failure. (5.3).
- Monitor heart rate and rhythm for bradycardia, including sinus pause, heart block, severe bradycardia, and cardiac arrest in patients receiving Labetalol Hydrochloride Tablets. (5.2)
- Beta-blockade can depress myocardial contractility and precipitating more severe failure. Avoid use in patients with overt heart failure. (5.3)
- Acute exacerbation of coronary artery disease upon cessation of therapy. Do not abruptly discontinue. (5.4)
- Avoid use in patients with bronchospastic disease. (5.5)
- Beta‑adrenergic blockade may prevent the appearance of premonitory signs and symptoms (e.g., tachycardia) of acute hypoglycemia. (5.6)
- Exacerbation of pheochromocytoma: Paradoxical increases in blood pressure may occur. (5.7)
- Hepatic necrosis and death have been reported. If the patient develops signs or symptoms of liver injury, institute appropriate treatment and investigate the probable cause. (5.8)
- Do not routinely withdraw chronic beta blocker therapy prior to surgery. (5.10)

6 ADVERSE REACTIONS

Most commonly observed adverse reactions: fatigue, nausea, dizziness (6.1)

To report SUSPECTED ADVERSE REACTIONS, contact Innogenix, LLC at 1-844-466-6469 or FDA at 1-800-FDA-1088 or www.fda.gov/medwatch.

7 DRUG INTERACTIONS

- Concomitant use with negative chronotropes can increase risk of bradycardia (7.1)
- Beta blockers antagonize the bronchodilator effect of beta-receptor agonists. (7.2)
- Increase hypotension may occur with halothane anesthesia. (7.3)
- Nitroglycerin may result in additional hypotensive effects. (7.4)

FULL PRESCRIBING INFORMATION

1 INDICATIONS AND USAGE

Labetalol Hydrochloride is indicated in the management of hypertension, to lower blood pressure. Lowering blood pressure reduces the risk of fatal and nonfatal cardiovascular events, primarily strokes and myocardial infarctions. These benefits have been seen in controlled trials of antihypertensive drugs from a wide variety of pharmacologic classes including beta adrenergic blockers.

Control of high blood pressure should be part of comprehensive cardiovascular risk management, including, as appropriate, lipid control, diabetes management, antithrombotic therapy, smoking cessation, exercise, and limited sodium intake. Many patients will require more than one drug to achieve blood pressure goals. For specific advice on goals and management, see published guidelines, such as those of the National High Blood Pressure Education Program’s Joint National Committee on Prevention, Detection, Evaluation, and Treatment of High Blood Pressure (JNC).

Numerous antihypertensive drugs, from a variety of pharmacologic classes and with different mechanisms of action, have been shown in randomized controlled trials to reduce cardiovascular morbidity and mortality, and it can be concluded that it is blood pressure reduction, and not some other pharmacologic property of the drugs, that is largely responsible for those benefits. The largest and most consistent cardiovascular outcome benefit has been a reduction in the risk of stroke, but reductions in myocardial infarction and cardiovascular mortality also have been seen regularly.

Elevated systolic or diastolic pressure causes increased cardiovascular risk, and the absolute risk increase per mmHg is greater at higher blood pressures, so that even modest reductions of severe hypertension can provide substantial benefit. Relative risk reduction from blood pressure reduction is similar across populations with varying absolute risk, so the absolute benefit is greater in patients who are at higher risk independent of their hypertension (for example, patients with diabetes or hyperlipidemia), and such patients would be expected to benefit from more aggressive treatment to a lower blood pressure goal.

Some antihypertensive drugs have smaller blood pressure effects (as monotherapy) in black patients, and many antihypertensive drugs have additional approved indications and effects (e.g., on angina, heart failure, or diabetic kidney disease). These considerations may guide selection of therapy.

Labetalol Hydrochloride Tablets may be used alone or in combination with other antihypertensive agents, especially thiazide and loop diuretics.

2 DOSAGE AND ADMINISTRATION

2.1 Recommended Dosage

Labetalol Hydrochloride dosage must be individualized.

The recommended initial dosage of labetalol hydrochloride is 100 mg twice daily. Adjust dosage in increments of 100 mg twice daily at 2- to 3-day intervals based on response. The recommended maintenance dosage of labetalol hydrochloride is between 200 and 400 mg twice daily.

3 DOSAGE FORMS AND STRENGTHS

Labetalol Hydrochloride Tablets are available in the following strengths:

- 100 mg - Round, beige, film-coated tablets, plain on one side, scored and debossed with “I/126” on the other side.
- 200 mg - Round, white, film-coated tablets, plain on one side, scored and debossed with “I/127” on the other side.
- 300 mg - Round, blue, film-coated tablets, plain on one side and debossed with “I/130” on the other side.

4 CONTRAINDICATIONS

Labetalol Hydrochloride Tablets are contraindicated in patients with:

- bronchial asthma or obstructive airway disease
- decompensated heart failure
- greater than first degree heart block
- cardiogenic shock
- severe bradycardia
- Hypersensitivity reactions, including anaphylaxis, to labetalol
- non-dihydropyridine calcium-channel antagonists

5 WARNINGS AND PRECAUTIONS

5.1 Hypotension

Monitor patients for symptomatic postural hypotension and syncope after initial dosing or dose increments with Labetalol Hydrochloride Tablets. Elderly patients are generally more likely than younger patients to experience orthostatic symptoms [see Dosage and Administration (2.1), Use in Specific Populations (8.5), Clinical Pharmacology (12.2)].

5.2 Bradycardia

Bradycardia, including sinus pause, heart block, severe bradycardia, and cardiac arrest have occurred with the use of beta blockers. Monitor heart rate and rhythm in patients receiving Labetalol Hydrochloride Tablets.

5.3 Cardiac Failure

Sympathetic stimulation is a vital component supporting circulatory function in congestive heart failure. Beta‑blockade carries a potential hazard of further depressing myocardial contractility and precipitating more severe failure. Avoid Labetalol Hydrochloride Tablets in patients with overt congestive heart failure. If patients develop signs or symptoms of heart failure during administration, discontinue Labetalol Hydrochloride Tablets and treat appropriately.

5.4 Ischemic Heart Disease

Abrupt cessation of therapy with beta blocking agents in patients with coronary artery disease can cause exacerbations of angina pectoris and, in some cases, myocardial infarction has been reported. Therefore, even in the absence of overt angina pectoris, after the discontinuation of Labetalol Hydrochloride Tablets observe patients for development or worsening of angina. If patient experiences angina or angina markedly worsens or if acute coronary insufficiency develops, promptly reinstitute Labetalol Hydrochloride Tablets and manage as unstable angina.

5.5 Reactive Airway Disease and Nonallergic Bronchospasm

Avoid use in patients with reactive airways disease. If Labetalol Hydrochloride Tablets are used, use the smallest effective dose, to minimize inhibition of endogenous or exogenous beta agonists.

5.6 Hypoglycemia

Beta-blockers may prevent early warning signs of hypoglycemia, such as tachycardia, and increase the risk for severe or prolonged hypoglycemia at any time during treatment, especially in patients with diabetes mellitus or children and patients who are fasting (i.e., surgery, not eating regularly, or are vomiting). If severe hypoglycemia occurs, patients should be instructed to seek emergency treatment.

5.7 Use in Patients with Pheochromocytoma

Labetalol hydrochloride has been shown to be effective in lowering blood pressure and relieving symptoms in patients with pheochromocytoma; higher than usual doses may be required. However, paradoxical hypertensive responses have been reported in a few patients with this tumor; therefore, blood pressure when administering labetalol hydrochloride to patients with pheochromocytoma.

5.8 Hepatic Injury

Severe hepatocellular injury occurs rarely with labetalol therapy. The hepatic injury is usually reversible, but hepatic necrosis and death have been reported. If the patient develops signs or symptoms of liver injury, institute appropriate treatment and investigate the probable cause. Do not restart labetalol in patients without another explanation for the observed liver injury.

5.9 Use in Patients at Risk of Severe Acute Hypersensitivity Reactions

Patients at risk of anaphylactic reactions may be more reactive to allergen exposure (accidental, diagnostic, or therapeutic). Patients using beta-blockers may be unresponsive to the usual doses of epinephrine used to treat anaphylactic or anaphylactoid reactions. Avoid Labetalol Hydrochloride Tablets in patients at high risk of anaphylactic reactions.

5.10 Major Surgery

Do not routinely withdraw chronic beta blocker therapy prior to surgery. The effect of labetalol’s alpha adrenergic activity has not been evaluated in this setting.

A synergism between labetalol hydrochloride and halothane anesthesia has been shown [ see Drug Interactions (7.3)].

5.11 Intraoperative Floppy Iris Syndrome (IFIS)

IFIS has been observed during cataract surgery in some patients treated with alpha-1 blockers (labetalol is an alpha/beta blocker). This variant of small pupil syndrome is characterized by the combination of a flaccid iris that billows in response to intraoperative irrigation currents, progressive intraoperative miosis despite preoperative dilation with standard mydriatic drugs, and potential prolapse of the iris toward the phacoemulsification incisions. Inform the patient’s ophthalmologist to be prepared for possible modifications to the surgical technique, such as the utilization of iris hooks, iris dilator rings, or viscoelastic substances.

6 ADVERSE REACTIONS

- Hypotension [see Warnings and Precautions (5.1)
- Bradycardia [see Warnings and Precautions (5.2)]
- Cardiac failure [see Warnings and Precautions (5.3)]
- Ischemic heart disease [see Warnings and Precautions (5.4)]
- Nonallergic bronchospasm [see Warnings and Precautions (5.5))]
- Use in patients with pheochromocytoma [see Warnings and Precautions (5.7)]
- Hepatic injury [see Warnings and Precautions (5.8)]
- Risk of severe acute hypersensitivity reaction [see Warnings and Precautions (5.9)]

6.1 Clinical Trials Experience

Adverse Reactions Resulting in Discontinuation of Treatment

Because clinical trials are conducted under widely varying conditions, adverse reaction rates observed in the clinical trials of a drug cannot be directly compared to rates in the clinical trials of another drug and may not reflect the rates observed in practice.

In controlled clinical trials of 3 to 4 months' duration, discontinuation of Labetalol Hydrochloride Tablets due to one or more adverse effects was required in 7% of all patients.

The incidence rates of adverse reactions listed in Table 1 were derived from multicenter, controlled clinical trials comparing labetalol hydrochloride and placebo over treatment periods of 3 and 4 months.

Table 1: Adverse Reactions Occurring in at Least 2% of Patients and More Frequent on Labetalol

 | Labetalol HCl (n=227) | Placebo (n=98)
Body as a whole
Fatigue | 5% | 0%
Headache | 2% | 1%
Gastrointestinal
Nausea | 6% | 1%
Dyspepsia | 3% | 1%
Central and Peripheral Nervous Systems
Dizziness | 11% | 3%
Autonomic Nervous System
Nasal stuffiness | 3% | 0%
Respiratory
Dyspnea | 2% | 0%
Special Senses
Vertigo | 2% | 1%

The adverse effects were reported spontaneously and are representative of the incidence of adverse effects that may be observed in a properly selected hypertensive patient population, i.e., a group excluding patients with bronchospastic disease, overt congestive heart failure, or other contraindications to beta‑blocker therapy.

Clinical trials also included studies utilizing daily doses up to 2,400 mg in more severely hypertensive patients. Certain of the side effects increased with increasing dose, as shown in Table 2 that depicts the entire US therapeutic trials data base for adverse reactions that are clearly or possibly dose related.

7 DRUG INTERACTIONS

7.1 Negative Chronotopes

Digitalis glycosides, diltiazem, verapamil, and beta-blockers slow atrioventricular conduction and decrease heart rate. Concomitant use with negative chronotropes can increase the risk of bradycardia or hypotension [see Warnings and Precautions (5.2)]. Coadministration of labetalol HCl with non-dihydropyridine calcium-channel antagonists (e.g., verapamil) is contraindicated [see Contraindications (4)].

7.2 Bronchodilators

Labetalol HCl antagonizes the bronchodilatory effect of beta-receptor agonist drugs; therefore, labetalol HCl is contraindicated in patients with bronchial asthma [see Contraindications (4)].

7.3 Anesthesia

Synergism has been shown between halothane anesthesia and intravenously administered labetalol. During controlled hypotensive anesthesia using labetalol in association with halothane, high concentrations (3% or above) of halothane should not be used because the degree of hypotension will be increased and because of the possibility of a large reduction in cardiac output and an increase in central venous pressure.

7.4 Nitroglycerin

Coadministration of labetalol HCl and nitroglycerine will have an additive effect in lowering blood pressure. Additionally, labetalol HCl blunts the reflex tachycardia produced by nitroglycerin. If labetalol HCl is used in patients with angina pectoris on nitroglycerin, monitor patients’ blood pressure and adjust labetalol dose as needed. In these patients, avoid initiating Labetalol Hydrochloride Tablets.

7.5 Drug/Laboratory Test Interactions

The presence of labetalol metabolites in the urine may result in falsely elevated levels of urinary catecholamines, metanephrine, normetanephrine, and vanillylmandelic acid (VMA) when measured by fluorimetric or photometric methods. In screening patients suspected of having a pheochromocytoma and being treated with labetalol, a specific method, such as a high-performance liquid chromatographic assay with solid phase extraction should be employed in determining levels of catecholamines.

Labetalol has also been reported to produce a false positive test for amphetamine when screening urine for the presence of drugs using the commercially available assay methods. When patients being treated with labetalol have a positive urine test for amphetamine using these techniques, confirm using more specific methods, such as a gas chromatographic mass spectrometer technique.

8 USE IN SPECIFIC POPULATIONS

8.1 Pregnancy

Risk Summary

The extensive experience with use of labetalol in pregnant women, based on published interventional and observational studies, has not identified a drug-associated risk for major birth defects, miscarriage, or adverse maternal or fetal outcomes (see Data). Untreated hypertension during pregnancy can lead to serious adverse outcomes for the mother and the fetus (see Clinical Considerations). In animal reproductive studies, oral administration of labetalol to pregnant rats and rabbits during organogenesis at doses up to approximately six and four times the maximum recommended human dose (MRHD), respectively, resulted in no fetal malformations; however, increased fetal resorptions were seen in both species at doses approximating the MRHD (see Data).

In the U.S. general population, the estimated background risk of major birth defects and miscarriage in clinically recognized pregnancies is 2% to 4% and 15% to 20%, respectively.

Clinical Consideration

Disease-Associated Maternal and/or Embryo/Fetal Risk

Hypertension in pregnancy increase the maternal risk for pre-eclampsia, gestational diabetes, premature delivery, and delivery complications (e.g., need for cesarean section, and post-partum hemorrhage). Hypertension increases the fetal risk for intrauterine growth restriction and intrauterine death. Pregnant women with hypertension should be carefully monitored and managed accordingly.

Fetal/Neonatal Adverse Reactions

Labetalol crosses the placenta. Newonates born to mothers who are receiving labetalol during pregnancy, may be at risk for hypotension, bradycardia, hypoglycemia, and respiratory depression. Neonates should be monitored for symptoms of hypotension, bradycardia, hypoglycemia and respiratly depression and mange accordingly.

Data

Human Data

Data from published interventional and observational studies did not demonstrate an association between major congenital malformations and the use of labetalol in pregnancy, however, most studies reported the maternal use of intravenous labetalol occurring after 20 weeks gestation. The published literature has reported inconsistent findings of intrauterine growth retardation, preterm birth and perinatal mortality with maternal use of labetalol during pregnancy; however, these studies have methodological limitations hindering interpretation. These studies cannot definitively establish the absence of risk during pregnancy.

Animal Data

Teratogenic studies were performed with labetalol in rats and rabbits at oral doses up to approximately six and four times the maximum recommended human dose (MRHD), respectively. No

reproducible evidence of fetal malformations was observed. Increased fetal resorptions were seen in both species at doses approximating the MRHD.

A teratology study performed with labetalol in rabbits at intravenous doses up to 1.7 times the MRHD revealed no evidence of drug-related harm to the fetus.

Oral administration of labetalol to rats during late gestation through weaning at doses of two to four times the MRHD caused a decrease in neonatal survival.

8.2 Lactation

Risk Summary

Available published data report the presence of labetalol in human milk at low levels. There are no data on the effects on the breastfed infant and on milk production. The developmental and health benefits of breastfeeding should be considered along with the mother's clinical need for labetalol and any potential adverse effects on the breastfed infant from labetalol or from the underlying maternal condition.

8.4 Pediatric Use

Safety and effectiveness in pediatric patients have not been established.

8.5 Geriatric Use

Pharmacokinetic studies indicate that the elimination of labetalol is reduced in elderly patients. Although elderly patients may initiate therapy at the currently recommended dosage of 100 mg twice daily, elderly patients will generally require lower maintenance dosages than nonelderly patients.

10 OVERDOSAGE

Overdosage with labetalol hydrochloride causes excessive hypotension that is posture sensitive and, sometimes, excessive bradycardia. Patients should be placed supine and their legs raised if necessary to improve the blood supply to the brain. Treat symptoms of overdose with standard supportive care. If overdosage with labetalol hydrochloride follows oral ingestion, gastric lavage or pharmacologically induced emesis (using syrup of ipecac) may be useful for removal of the drug shortly after ingestion. Treat symptoms of overdose with standard supportive care.

Neither hemodialysis nor peritoneal dialysis removes a significant amount of labetalol hydrochloride from the general circulation (<1%).

The oral LD50 value of labetalol hydrochloride in the mouse is approximately 600 mg/kg and in the rat is >2 g/kg. The IV LD50in these species is 50 mg/kg to 60 mg/kg.

11 DESCRIPTION

Labetalol hydrochloride tablets, USP are an adrenergic receptor blocking agent that has both selective alpha1-adrenergic and nonselective beta-adrenergic receptor blocking actions in a single substance.

Labetalol hydrochloride, USP is a racemate, chemically designated as 2-hydroxy-5-[1-hydroxy-2-[(1-methyl-3-phenylpropyl)amino]ethyl] benzamide monohydrochloride, and it has the following structure:

Labetalol hydrochloride, USP has the molecular formula C19H24N2O3•HCl and a molecular weight of 364.87. It has two asymmetric centers and therefore exists as a molecular complex of two diastereoisomeric pairs. Dilevalol, the R,R’ stereoisomer, makes up 25% of racemic labetalol.

Labetalol hydrochloride, USP is a white or off-white crystalline powder, soluble in water.

Labetalol hydrochloride tablets, USP, for oral administration, contain 100 mg, 200 mg or 300 mg labetalol hydrochloride, USP.

In addition, each 100 mg tablet contains the following inactive ingredients: anhydrous lactose, carnauba wax, hypromellose, magnesium stearate, polyethylene glycol, polysorbate 80, pregelatinized starch (corn), red iron oxide, titanium dioxide and yellow iron oxide.

In addition, each 200 mg tablet contains the following inactive ingredients: anhydrous lactose, carnauba wax, hypromellose, magnesium stearate, polydextrose, polyethylene glycol, pregelatinized starch (corn), titanium dioxide and triacetin.

In addition, each 300 mg tablet contains the following inactive ingredients: anhydrous lactose, carnauba wax, FD&C Blue #2, hypromellose, magnesium stearate, polyethylene glycol, polysorbate 80, pregelatinized starch (corn), titanium dioxide.

12 CLINICAL PHARMACOLOGY

12.1 Mechanism of Action

Labetalol hydrochloride combines both selective, competitive, alpha1‑adrenergic blocking and nonselective, competitive, beta‑adrenergic blocking activity. The ratios of alpha- to beta‑blockade have been estimated to be approximately 1:3 and 1:7 following oral and intravenous (IV) administration, respectively.

12.2 Pharmacodynamics

The capacity of labetalol hydrochloride to block alpha receptors in man has been demonstrated by attenuation of the pressor effect of phenylephrine and by a significant reduction of the pressor response caused by immersing the hand in ice cold water ("cold pressor test"). Labetalol hydrochloride's beta1 receptor blockade in man was demonstrated by a small decrease in the resting heart rate, attenuation of tachycardia produced by isoproterenol or exercise, and by attenuation of the reflex tachycardia to the hypotension produced by amyl nitrite. Beta2 receptor blockade was demonstrated by inhibition of the isoproterenol induced fall in diastolic blood pressure. Both the alpha- and beta blocking actions of orally administered labetalol hydrochloride contribute to a decrease in blood pressure in hypertensive patients. Labetalol hydrochloride consistently, in dose related fashion, blunted increases in exercise induced blood pressure and heart rate, and in their double product. The pulmonary circulation during exercise was not affected by labetalol hydrochloride dosing.

The effects on A‑V nodal refractoriness were inconsistent. Single oral doses of labetalol hydrochloride administered to patients with coronary artery disease had no significant effect on sinus rate, intraventricular conduction, or QRS duration. The atrioventricular (A‑V) conduction time was modestly prolonged in two of seven patients. In another study, IV labetalol hydrochloride slightly prolonged A‑V nodal conduction time and atrial effective refractory period with only small changes in heart rate.

Labetalol hydrochloride produces dose‑related falls in blood pressure without reflex tachycardia and without significant reduction in heart rate, presumably through a mixture of its alpha- and beta‑blocking effects. Hemodynamic effects are variable, with small, nonsignificant changes in cardiac output seen in some studies but not others, and small decreases in total peripheral resistance. Elevated plasma renins are reduced.

Due to the alpha1‑receptor blocking activity of labetalol hydrochloride, blood pressure is lowered more in the standing than in the supine position, and symptoms of postural hypotension (2%), including rare instances of syncope, can occur. Following oral administration, when postural hypotension has occurred, it has been transient and is uncommon when the recommended starting dose and titration increments are closely followed [see Dosage and Administration (2.1)]. Symptomatic postural hypotension is most likely to occur 2 to 4 hours after a dose, especially following the use of large initial doses or upon large changes in dose.

The peak effects of single oral doses of labetalol hydrochloride occur within 2 to 4 hours. The duration of effect depends upon dose, lasting at least 8 hours following single oral doses of 100 mg and more than 12 hours following single oral doses of 300 mg. The maximum, steady‑state blood pressure response upon oral, twice‑a‑day dosing occurs within 24 to 72 hours.

The antihypertensive effect of labetalol has a linear correlation with the logarithm of labetalol plasma concentration, and there is also a linear correlation between the reduction in exercise induced tachycardia occurring at 2 hours after oral administration of labetalol hydrochloride and the logarithm of the plasma concentration.

About 70% of the maximum beta‑blocking effect is present for 5 hours after the administration of a single oral dose of 400 mg with suggestion that about 40% remains at 8 hours.

12.3 Pharmacokinetics and Metabolism

Absorption

Labetalol hydrochloride is absorbed with peak plasma levels occurring 1 to 2 hours after oral administration.

The relative bioavailability of Labetalol Hydrochloride Tablets compared to an oral solution is 100%.

The absolute bioavailability (fraction of drug reaching systemic circulation) of labetalol when compared to an IV infusion is 25%; this is due to extensive "first-pass" metabolism. There is a linear relationship between oral doses of 100 mg to 3,000 mg and peak plasma levels.

Effect of Food

The absolute bioavailability of labetalol is increased when administered with food.

Distribution

Labetalol has been shown to cross the placental barrier in humans. Labetalol is approximately 50% protein bound.

Elimination

The plasma half-life of labetalol following oral administration is about 6 to 8 hours. Steady-state plasma levels of labetalol are reached by about the third day of dosing.

Metabolism

Metabolism of labetalol is mainly through conjugation to glucuronide metabolites.

Excretion

Approximately 55% to 60% of a dose appears in the urine as conjugates or unchanged labetalol within the first 24 hours of dosing. These metabolites are present in plasma and are excreted in the urine and, via the bile, into the feces. Neither hemodialysis nor peritoneal dialysis removes a significant amount of labetalol hydrochloride from the general circulation (<1%).

Specific Populations

Patients with Renal or Hepatic Impairment

In patients with decreased hepatic or renal function, the elimination half‑life of labetalol is not altered; however, the relative bioavailability in hepatically impaired patients is increased due to decreased "first‑pass" metabolism.

Drug Interaction Studies

Tricyclic Antidepressants

In one survey, 2.3% of patients taking labetalol hydrochloride in combination with tricyclic antidepressants experienced tremor, as compared to 0.7% reported to occur with labetalol hydrochloride alone. The contribution of each of the treatments to this adverse reaction is unknown, but the possibility of a drug interaction cannot be excluded.

Cimetidine

Cimetidine has been shown to increase the bioavailability of labetalol hydrochloride. Since this could be explained either by enhanced absorption or by an alteration of hepatic metabolism of labetalol hydrochloride, special care should be used in establishing the dose required for blood pressure control in such patients.

13 NONCLINICAL TOXICOLOGY

Carcinogenesis

Long‑term oral dosing studies with labetalol hydrochloride for 18 months in mice and for 2 years in rats showed no evidence of carcinogenesis. Studies with labetalol hydrochloride using dominant lethal assays in rats and mice and exposing microorganisms according to modified Ames tests showed no evidence of mutagenesis.

16 HOW SUPPLIED/STORAGE AND HANDLING

Labetalol Hydrochloride Tablets, USP, for oral administration, are available as

100 mg Round, beige film-coated tablets, plain on one side, scored and debossed with “I/126” on the other side:

- NDC 71335-3065-1: 30 Tablets in a Bottle
- NDC 71335-3065-2: 90 Tablets in a Bottle
- NDC 71335-3065-3: 60 Tablets in a Bottle
- NDC 71335-3065-4: 120 Tablets in Bottle
- NDC 71335-3065-5: 10 Tablets in a Bottle

Labetalol Hydrochloride Tablets, USP should be stored at 20° to 25°C (68° to 77°F) [See USP Controlled Room Temperature].

Dispense in a tight, light-resistant container as defined in the USP with a child-resistant closure as required.

Repackaged/Relabeled by:
Bryant Ranch Prepack
Burbank, CA 91504

17 PATIENT COUNSELING INFORMATION

- Advise patients to not interrupt or discontinue using Labetalol Hydrochloride Tablets without advice from their healthcare provider
- Advise patients to contact their healthcare provider about any signs or symptoms of impending cardiac failure or hepatic dysfunction [see Warnings and Precautions (5.3,5.8)]
- Inform patients or caregivers that there is a risk of hypoglycemia when Labetalol Hydrochloride Tablets is given to patients who are fasting or who are vomiting. Monitor for symptoms of hypoglycemia [ see Warnings and Precautions (5.6)].

PACKAGE LABEL

Labetalol Hydrochloride 100mg Tablets